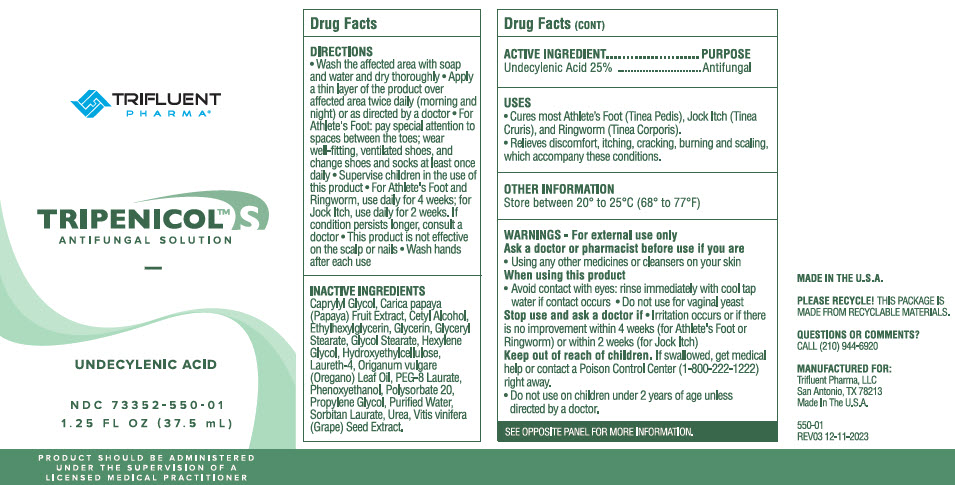 DRUG LABEL: Tripenicol S
NDC: 73352-550 | Form: SOLUTION
Manufacturer: Trifluent Pharma LLC
Category: otc | Type: HUMAN OTC DRUG LABEL
Date: 20251014

ACTIVE INGREDIENTS: UNDECYLENIC ACID 0.25 g/1 mL
INACTIVE INGREDIENTS: WATER; HYDROXYETHYL CELLULOSE, UNSPECIFIED; GLYCERIN; UREA; PROPYLENE GLYCOL; OREGANO LEAF OIL; GRAPE SEED OIL; PAPAYA SEED OIL; CETYL ALCOHOL; GLYCOL STEARATE; PEG-8 LAURATE; SORBITAN MONOLAURATE; POLYSORBATE 20; GLYCERYL MONOSTEARATE; LAURETH-4; PHENOXYETHANOL; CAPRYLYL GLYCOL; ETHYLHEXYLGLYCERIN; HEXYLENE GLYCOL

Tripenicol™ S

DRUG FACTS

ACTIVE INGREDIENT

Undecylenic Acid 25%

PURPOSE

Antifungal

USES

- Cures most Athlete's Foot (Tinea Pedis), Jock Itch (Tinea Cruris), and Ringworm (Tinea Corporis).
- Relives discomfort, itching, cracking, burning and scaling, which accompany these conditions.

OTHER INFORMATION

Store between 20° to 25°C (68° to 77°F)

WARNINGS

For external use only

Ask a doctor or pharmacist before use if you are

- Using any other medicines or cleansers on your skin

When using this product

- Avoid contact with eyes: rinse immediately with cool tap water if contact occurs.
- Do not use for vaginal yeast.

Stop use and ask a doctor if

- Irritation occurs or if there is no improvement within 4 weeks (for Athlete's Foot or Ringworm) or within 2 weeks (for Jock Itch)

Keep out of reach of children. If swallowed, get medical help or contact a Poison Control Center (1-800-222-1222) right away.

- Do not use on children under two years of age unless directed by a doctor.

DIRECTIONS

- Wash the affected area with soap and water and dry thoroughly
- Apply a thin layer of the product over affected area twice daily (morning and night) or as directed by a doctor
- For Athlete's Foot: pay special attention to spaces between the toes; wear well-fitting, ventilated shoes and change shoes and socks at least once daily
- Supervise children in the use of this product.
- For Athlete's Foot and Ringworm, use daily for 4 weeks; for Jock Itch, use daily for 2 weeks. If condition persists longer, consult a doctor.
- This product is not effective on the scalp or nails.
- Wash hands after each use.

INACTIVE INGREDIENTS

Caprylyl Glycol, Carica papaya (Papaya) Fruit Extract, Cetyl Alcohol, Ethylhexylglycerin, Glycerin, Glyceryl Stearate, Glycol Stearate, Hexylene Glycol, Hydroxyethylcellulose, Laureth-4, Origanum vulgare (Oregano) Leaf Oil, PEG-8 Laurate, Phenoxyethanol, Polysorbate 20, Propylene Glycol, Purified Water, Sorbitan Laurate, Urea, Vitis vinifera (Grape) Seed Extract.

QUESTIONS OR COMMENTS?

CALL (210) 944-6920

PRINCIPAL DISPLAY PANEL - 37.5 mL Bottle Label

TRIFLUENT
PHARMA®

TRIPENICOL™ S
ANTIFUNGAL SOLUTION

UNDECYLENIC ACID

NDC 73352-550-01

1.25 FL OZ (37.5 mL)